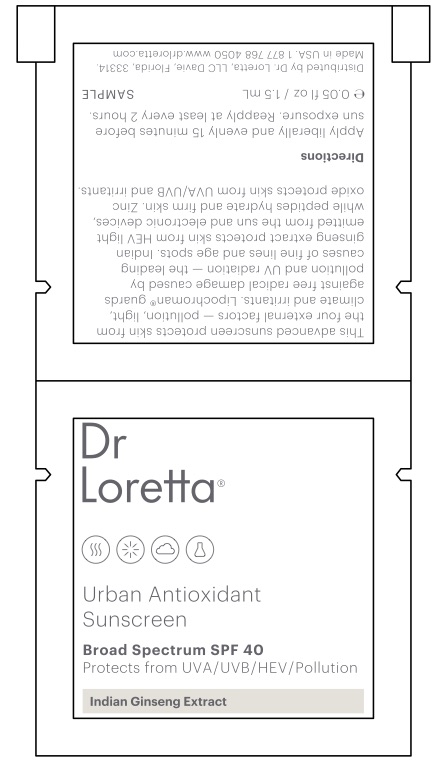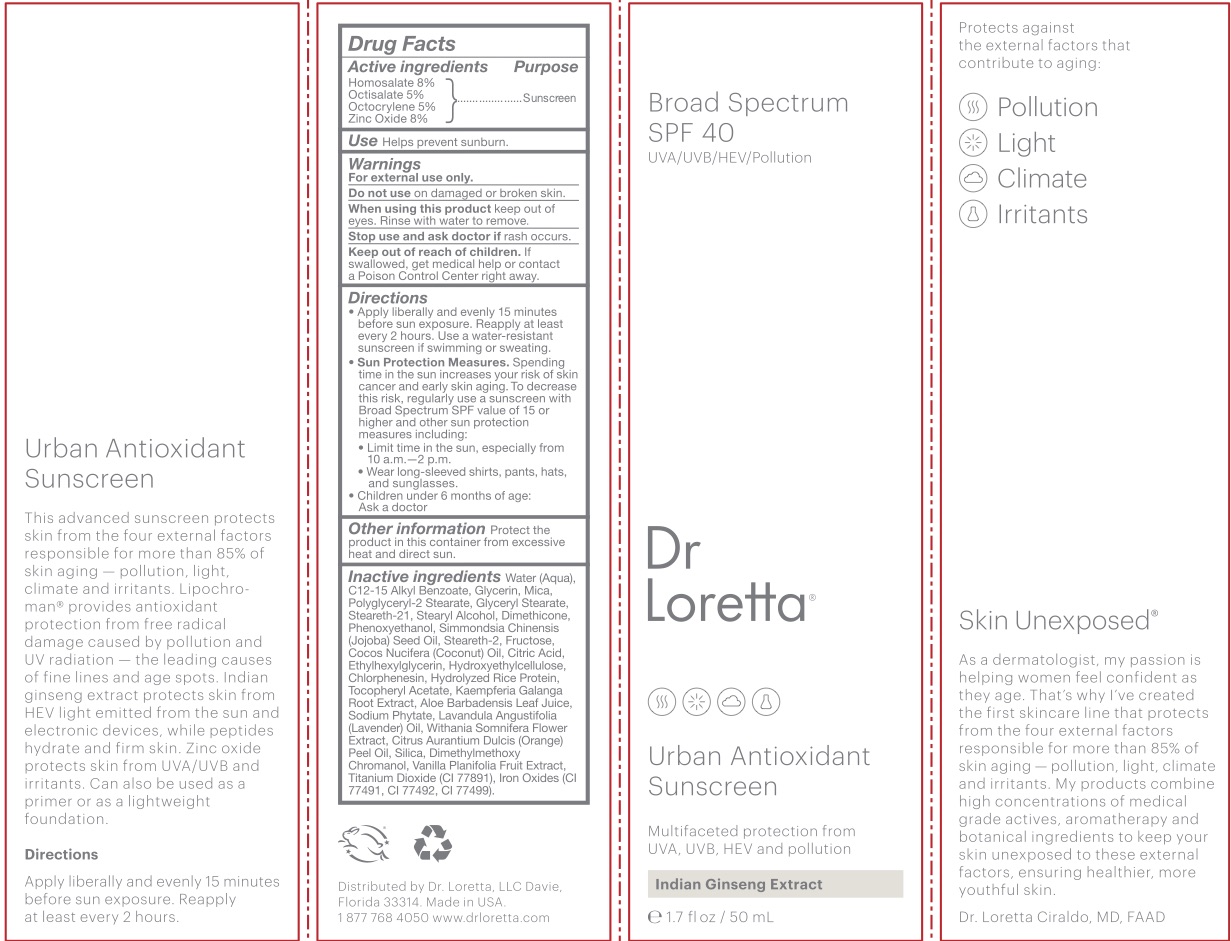 DRUG LABEL: Urban Antioxidant Sunscreen SPF 40
NDC: 71501-1902 | Form: CREAM
Manufacturer: Dr. Loretta, LLC
Category: otc | Type: HUMAN OTC DRUG LABEL
Date: 20250415

ACTIVE INGREDIENTS: HOMOSALATE 80 mg/1 mL; OCTOCRYLENE 50 mg/1 mL; ZINC OXIDE 80 mg/1 mL; OCTISALATE 50 mg/1 mL
INACTIVE INGREDIENTS: STEARETH-2; ETHYLHEXYLGLYCERIN; CHLORPHENESIN; FERRIC OXIDE RED; SILICON DIOXIDE; TITANIUM DIOXIDE; .ALPHA.-TOCOPHEROL ACETATE; KAEMPFERIA GALANGA ROOT; ALOE VERA LEAF; PHYTATE SODIUM; WATER; GLYCERYL MONOSTEARATE; STEARETH-21; MICA; ALKYL (C12-15) BENZOATE; GLYCERIN; POLYGLYCERYL-2 STEARATE; VANILLA; DIMETHYLMETHOXY CHROMANOL; DIMETHICONE; COCONUT OIL; CITRIC ACID MONOHYDRATE; STEARYL ALCOHOL; PHENOXYETHANOL; JOJOBA OIL; FRUCTOSE; ENGLISH LAVENDER OIL; WITHANIA SOMNIFERA FLOWER; ORANGE OIL

Urban Antioxidant Sunscreen SPF 40

ACTIVE INGREDIENT

Homosalate 8% Octisalate 5% Octocrylene 5% Zinc Oxide 8%

PURPOSE

Sunscreen

Use

Helps prevent sunburn.

INACTIVE INGREDIENT

Water C12-15 Alkyl Benzoate Glycerin Mica Polyglyceryl-2 Stearate Glyceryl Stearate Steareth-21 Stearyl Alcohol Dimethicone Phenoxyethanol Simmondsia Chinensis (Jojoba) Seed Oil Steareth-2 Fructose Cocos Nucifera (Coconut) Oil Citric Acid Ethylhexylglycerin Hydroxyethylcellulose Chlorphenesin Hydrolyzed Rice Protein Titanium Dioxide (CI 77891) Tocopheryl Acetate Kaempferia Galanga Root Extract Aloe Barbadensis Leaf Juice Sodium Phytate Lavandula Angustifolia (Lavender) Oil Withania Somnifera Flower Extract Iron Oxide (CI 77492) Iron Oxide (CI 77491) Citrus Aurantium Dulcis (Orange) Peel Oil Silica Dimethylmethoxy Chromanol Vanilla Planifolia Fruit Extract Iron Oxide (CI 77499)

WARNINGS

Warnings For external use only. Do not use on damaged or broken skin. When using this product keep out of eyes. Rinse with water to remove. Stop use and ask a doctor if rash occurs.

Keep out of reach of children.

If swallowed, get medical help or contact a Poison Control Center right away.

DOSAGE AND ADMINISTRATION

Directions • Apply liberally and evenly 15 minutes before sun exposure. • Reapply: at least every 2 hours • Use a water-resistant sunscreen if swimming or sweating. • Sun Protection Measures. Spending time in the sun increases your risk of skin cancer and early skin aging. To decrease this risk, regularly use a sunscreen with Broad Spectrum SPF value of 15 or higher and other sun protection measures including: • limit time in the sun, especially from 10 a.m.–2 p.m. • wear long-sleeved shirts, pants, hats and sunglasses • Children under 6 months of age: Ask a doctor.